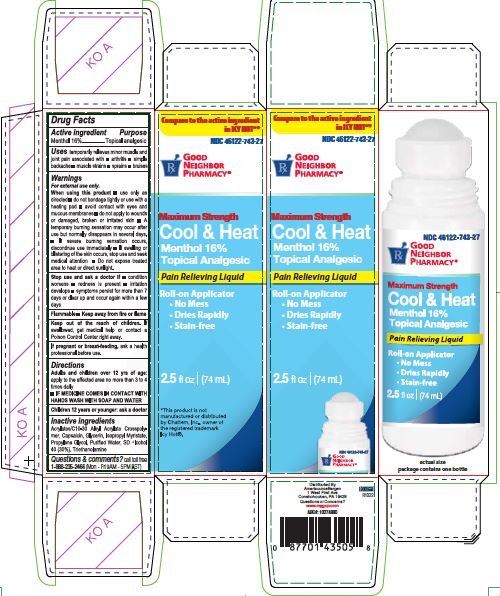 DRUG LABEL: Cool and Heat
NDC: 46122-743 | Form: LIQUID
Manufacturer: AMERISOURCE BERGEN
Category: otc | Type: HUMAN OTC DRUG LABEL
Date: 20241223

ACTIVE INGREDIENTS: MENTHOL 16 mg/100 mL
INACTIVE INGREDIENTS: (C10-C30)ALKYL METHACRYLATE ESTER; PROPYLENE GLYCOL; TROLAMINE; ALCOHOL; CAPSAICIN; ISOPROPYL MYRISTATE; GLYCERIN; WATER

GNP Cool & Heat

Active ingredient

Menthol 16%

Purpose

Topical analgesic

Uses

temporarily relieves minor muscle and joint pain associated with ▪ arthritis ▪ simple backache ▪ muscle strains ▪ sprains ▪ bruises

Warnings

For external use only.

When using this product ▪ use only as directed ▪ do not bandage tightly or use with a heating pad ▪ avoid contact with eyes and mucous membranes ▪ do not apply to wounds or damaged, broken or irritated skin ▪ A temporary burning sensation may occur after use but normally disappears in several days. ▪ If a severe burning sensation occurs, discontinue use immediately ▪ If swelling or blistering of the skin occurs, stop use and seek and seek medical attention ▪ Do not expose treated area to hear or direct sunlight.

Stop use and ask a doctor

▪ condition worsens ▪ redness is present ▪ irritation develops ▪ symptoms persist for more than 7 days or clear up and occur again within a few days

Flammable ▪ Keep away from fire or flame

Keep out of reach of children. If swallowed, get medical help or contact a Poison Control Center right away.

PREGNANCY OR BREAST FEEDING

If pregnant or breast-feeding, ask a health professional before use.

Directions

Adults and children over 12 yrs of age: apply to the affected area no more than 3 to 4 times daily

▪ IF MEDICINE COMES IN CONTACT WITH HANDS WASH WITH SOAP AND WATER

Children 12 years or younger: ask a doctor

Inactive ingredients

Acrylates/C10-30 Alkyl Acrylate Crosspolymer, Capsaicin, Glycerin, Isopropyl Myristate, Propylene Glycol, Purified Water, SD Alcohol 40 (30%), Triethanolamine

Questions & comments?

call toll free 1-888-235-2466 (Mon - Fri 9AM - 5PM EST)

Carton label

NDC 46122-743-27

GOOD

NEIGHBOR
PHARMACY®

Maximum Strength

Cool & Heat

Menthol 16%

Topical Analgesic

Pain Relieving Liquid

Roll-on Applicator

No Mess
Dries Rapidly
Stain-free

2.5 fl oz (74mL)

actual size

package contains one bottle

*This product is not

manufactured or distributed

by Chattem Inc., owner of

the registered trademark

Icy Hot®.

Distributed By

AmerisourceBergen
1 West First Ave
Conshohocken, PA 19428
Questions or Concerns?
www.mygnp.com
ABC#: 10274880

L0000658

R1022